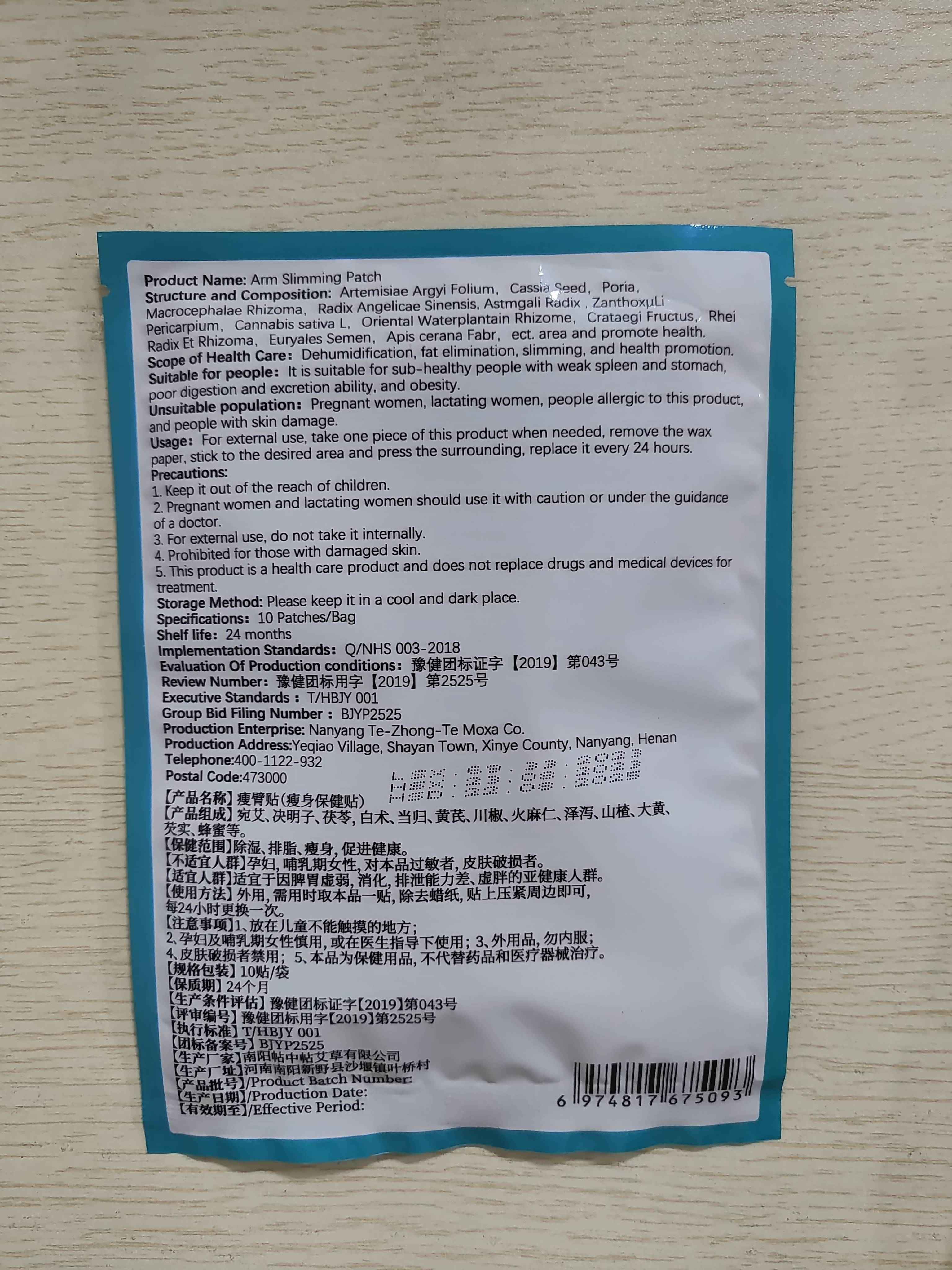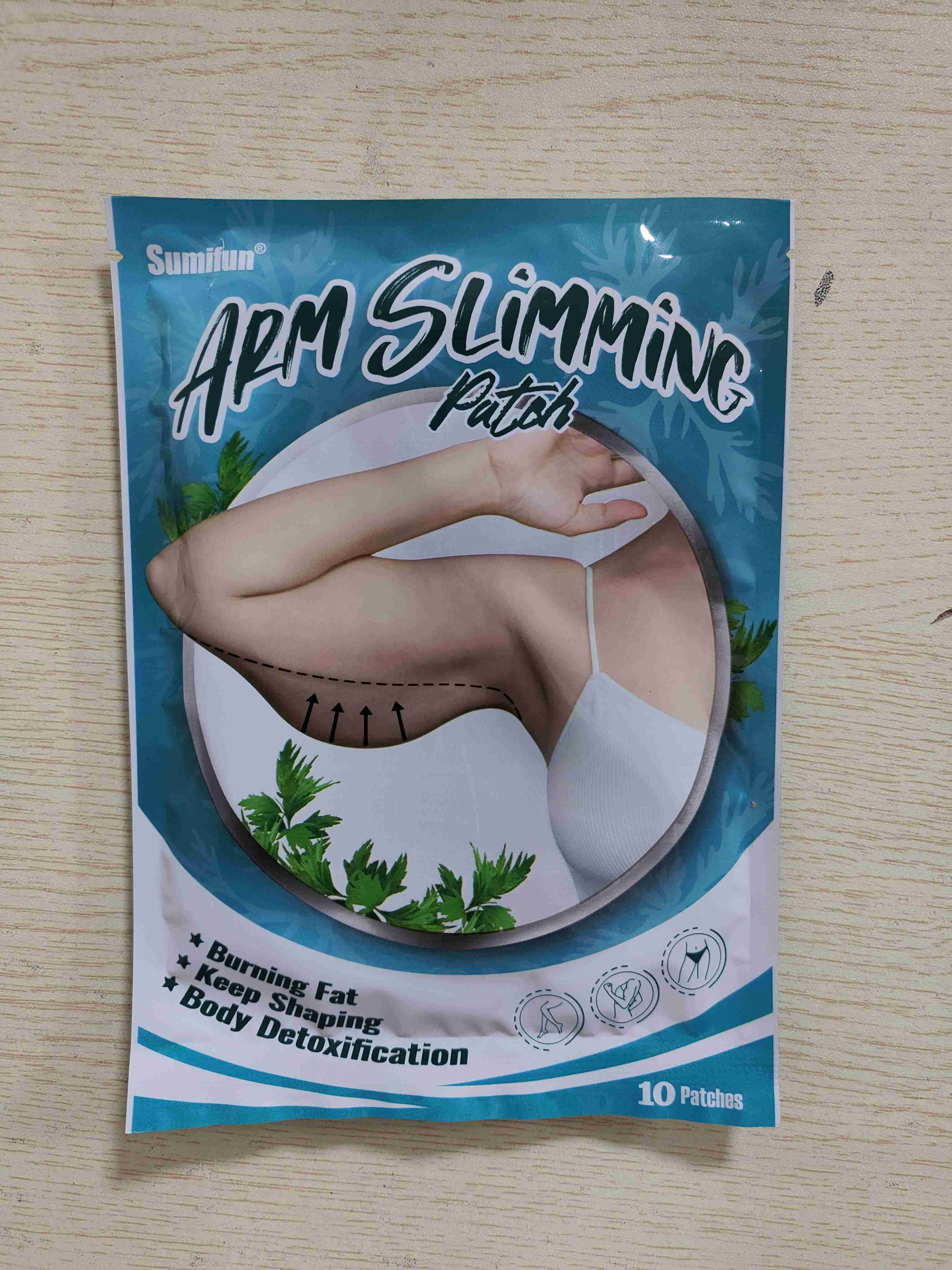 DRUG LABEL: Arm Slimming Patch
NDC: 83675-003 | Form: PATCH
Manufacturer: Guangzhou Hanhai Trading Co., Ltd
Category: otc | Type: HUMAN OTC DRUG LABEL
Date: 20230913

ACTIVE INGREDIENTS: ASTRAGALUS PROPINQUUS ROOT 13 g/100 1
INACTIVE INGREDIENTS: SENNA OBTUSIFOLIA SEED; ASARUM HETEROTROPOIDES ROOT; EURYALE FEROX SEED; ZANTHOXYLUM SCHINIFOLIUM FRUIT RIND; ANGELICA BISERRATA WHOLE; CRATAEGUS MONOGYNA FRUIT; ARTEMISIA ARGYI LEAF; FU LING; APIS CERANA WHOLE

Active Ingredient

Astmgali Radix 13.0%

Purpose

Burning Fat

Use

Arm Slimming Patch to help burning fat

Warnings

For external use only. Do not take it internally.

Keep Out Of Reach Of Children
Prohibited for those with damaged skin.

Do not use

Product shall not be eat

When Using

Do not stick around eyes and mouth,This product cannot replace drugs.

Stop Use

In case of adverse reactions, please stop using this product.If the symptoms.

Ask Doctor

ask doctor in case of adverse reactions.

Keep Oot Of Reach Of Children

Please do not place this product in a place where unconscious people can access it.

Directions

Take one piece of this product when needed, remove the waxpaper, stick to the desired area and press the surrounding, replace it every 24 hours.

Children should be used under adult supervision.

Other information

Store the product in a cool, dry and well-ventilated place

Avoid direct sunlight

Inactive ingredients

Artemisiae Argvi Folium

Cassia Seed

PoriaMacrocephalae Rhizoma

Radix Angelicae Sinensis

ZanthoxuLi Pericarpium

Crataegi Fructus

RheRadix

Et Rhizoma

Euryales Semen

Apis cerana Fabr